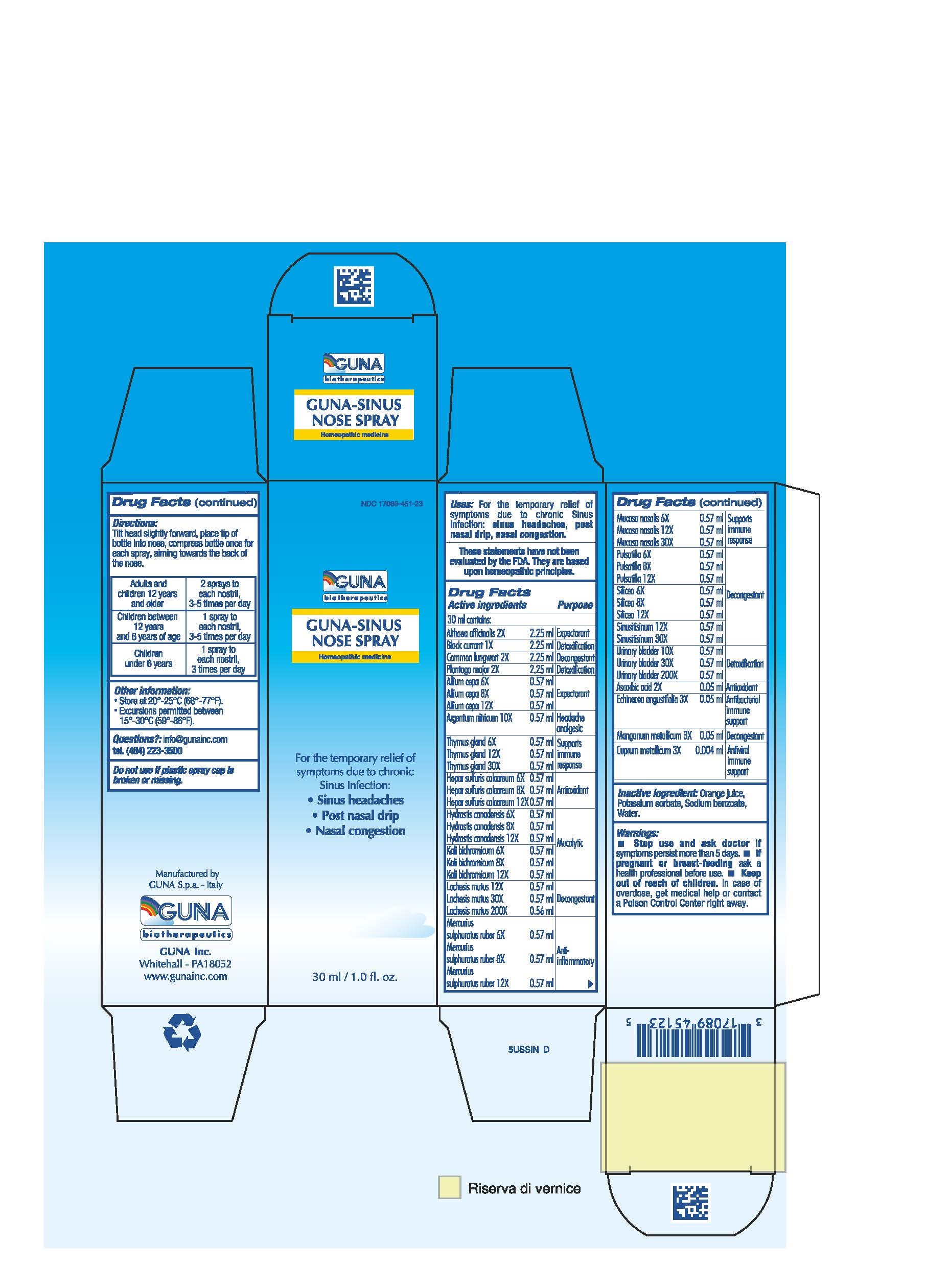 DRUG LABEL: GUNA-SINUS NOSE
NDC: 17089-451 | Form: SPRAY
Manufacturer: Guna spa
Category: homeopathic | Type: HUMAN OTC DRUG LABEL
Date: 20181222

ACTIVE INGREDIENTS: ONION 8 [hp_X]/30 mL; ALTHAEA OFFICINALIS LEAF 2 [hp_X]/30 mL; SILVER NITRATE 10 [hp_X]/30 mL; ASCORBIC ACID 2 [hp_X]/30 mL; BLACK CURRANT 1 [hp_X]/30 mL; LOBARIA PULMONARIA 2 [hp_X]/30 mL; COPPER 3 [hp_X]/30 mL; ECHINACEA ANGUSTIFOLIA 3 [hp_X]/30 mL; CALCIUM SULFIDE 8 [hp_X]/30 mL; GOLDENSEAL 8 [hp_X]/30 mL; POTASSIUM DICHROMATE 8 [hp_X]/30 mL; LACHESIS MUTA VENOM 30 [hp_X]/30 mL; MANGANESE 3 [hp_X]/30 mL; MERCURIC SULFIDE 8 [hp_X]/30 mL; SUS SCROFA NASAL MUCOSA 12 [hp_X]/30 mL; PLANTAGO MAJOR 2 [hp_X]/30 mL; PULSATILLA VULGARIS 8 [hp_X]/30 mL; SILICON DIOXIDE 8 [hp_X]/30 mL; SINUSITISINUM 30 [hp_X]/30 mL; SUS SCROFA THYMUS 12 [hp_X]/30 mL; SUS SCROFA URINARY BLADDER 30 [hp_X]/30 mL
INACTIVE INGREDIENTS: ORANGE JUICE 0.6 mL/30 mL; POTASSIUM SORBATE 0.03 mL/30 mL; WATER 15.9 mL/30 mL; SODIUM BENZOATE 0.03 mL/30 mL

GUNA-SINUS NOSE SPRAY

ACTIVE INGREDIENTS/PURPOSE

ALIUM CEPA 6X, 8X, 12X EXPECTORANT
ALTHEA OFFICINALIS 2X EXPECTORANT
ARGENTUM NITRICUM 10X HEADACHE ANALGESIC
ASCORBIC ACID 2X ANTIOXIDANT
BLACK CURRANT 1X DETOXIFICATION
COMMON LUNGWORT 2X DECONGESTANT
CUPRUM METALLICUM 3X ANTIVIRAL IMMUNE SUPPORT
ECHINACEA ANGUSTIFOLIA 3X ANTIBACTERIAL IMMUNE SUPPORT
HEPAR SULFURIS CALCAREUM 6X, 8X, 12X ANTIOXIDANT
HYDRASTIS CANADENSIS 6X, 8X, 12X MUCOLYTIC
KALI BICHROMICUM 6X, 8X, 12X MUCOLYTIC
LACHESIS MUTUS 12X, 30X, 200X DECONGESTANT
MANGANUM METALLICUM 3X DECONGESTANT
MERCURIUS SULPHURATUS RUBER 6X, 8X, 12X ANTI-INFLAMMATORY
MUCOSA NASALIS 6X, 12X, 30X SUPPORTS IMMUNE RESPONSE
PLANTAGO MAJOR 2X DETOXIFICATION
PULSATILLA 6X, 8X, 12X DECONGESTANT
SILICEA 6X, 8X, 12X DECONGESTANT
SINUSITISINUM 12X, 30X DECONGESTANT
THYMUS GLAND 6X, 12X, 30X SUPPORTS IMMUNE RESPONSE
URINARY BLADDER 10X, 30X, 200X DETOXIFICATION

USES

For the temporary relief of symptoms due to acute and chronic Sinus Infection:

- Sinus Headaches
- Post Nasal Drip
- Nasal Congestion

WARNINGS

- Stop use and ask doctor if symptoms persist more than 5 days.
- If pregnant or breast-feeding ask a health professional before use.
- Keep out of reach of children. In case of overdose, get medical help or contact a Poison Control Center right away.

PREGNANCY

If pregnant or breast-feeding ask a doctor before use

WARNINGS

Keep out of reach of children.

DIRECTIONS

Adults and children 12 years and older 2 sprays to each nostril, 3-5 times per day
Children between 12 years and 6 years of age 1 spray to each nostril, 3-5 times per day
Children under 6 years 1 spray to each nostril, 3 times per day

QUESTIONS

Questions?: info@gunainc.com
Tel. (484) 223-3500

Inactive ingredient: orange juice, potassium sorbate, sodium benzoate, water.

Directions:

tilt head slightly forward, place tip of bottle into nose, compress bottle once for each spray, aiming towards the back of the nose.

PRINCIPAL DISPLAY PANEL

1